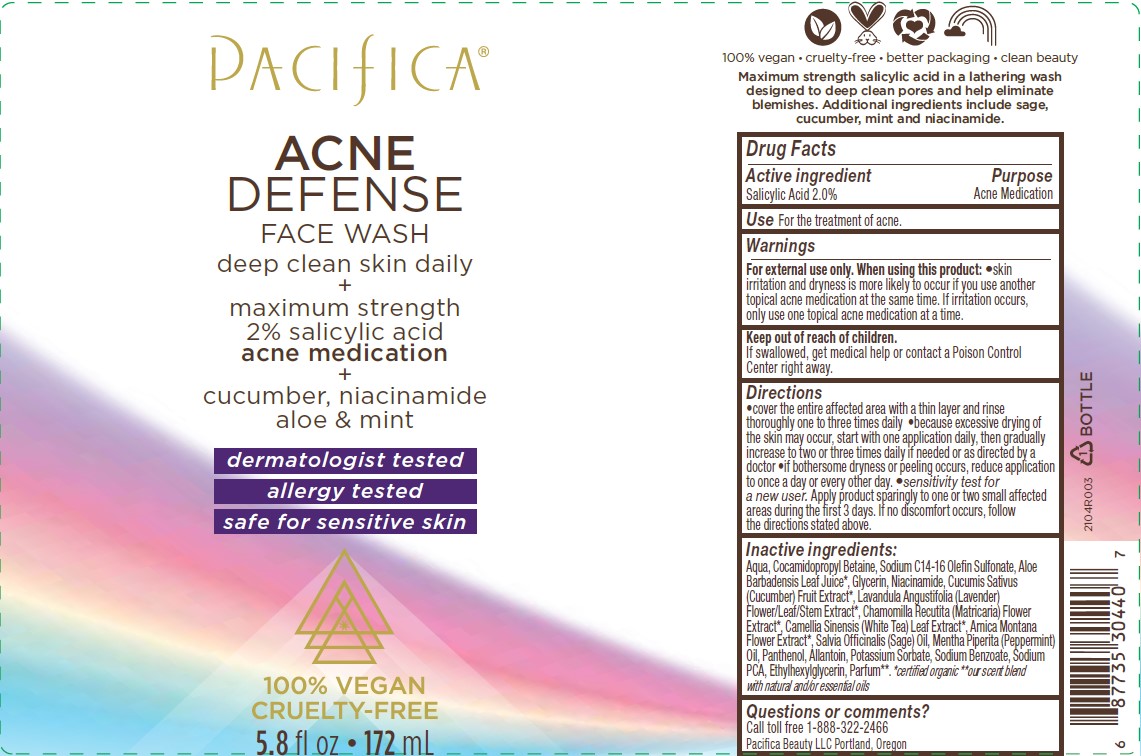 DRUG LABEL: Acne Defense Face Wash
NDC: 61197-120 | Form: LIQUID
Manufacturer: Pacifica Beauty, LLC
Category: otc | Type: HUMAN OTC DRUG LABEL
Date: 20250103

ACTIVE INGREDIENTS: SALICYLIC ACID 2 g/100 mL
INACTIVE INGREDIENTS: GLYCERIN; PANTHENOL; ETHYLHEXYLGLYCERIN; COCAMIDOPROPYL BETAINE; SODIUM C14-16 OLEFIN SULFONATE; LAVENDER OIL; WHITE TEA; ARNICA MONTANA FLOWER; SAGE OIL; PEPPERMINT OIL; ALLANTOIN; POTASSIUM SORBATE; SODIUM BENZOATE; CHAMOMILE FLOWER OIL; WATER; ALOE VERA LEAF; CUCUMBER FRUIT OIL; SODIUM PYRROLIDONE CARBOXYLATE; NIACINAMIDE

Acne Defense Face Wash

Active ingredient Purpose

Salicyic Acid 2.0% Acne Medication

Use

For the treatment of acne.

Warnings

For external use only. When using this product: skin irritation and dryness is more likely to occur if you use another topical acne medication at the same time. If irritation occurs, only use one topical acne medication at a time.

When using this product: skin irritation and dryness is more likely to occur if you use another topical acne medication at the same time. If irritation occurs, only use one topical acne medication at a time.

Keep out of reach of children

If swallowed, get medical help or contact a Poison Control Center right away.

Directions

Cover the entire affected area with a thin layer and rinse thoroughly one to three times daily. Because excessive drying of the skin may occur, start with one application daily, then gradually increase to two or three times daily if needed or as directed by a doctor. If bothersome dryness or peeling occurs, reduce application to once a day or every other day. Sensitivity test for a new user. Apply product sparingly to one or two small affected areas during the first 3 days. If no discomfort occurs, follow the directions stated above.

Inactive ingredients:

Aqua, Cocamidopropyl Betaine, Sodium C14-16 Olefin Sulfonate, Aloe Barbadensis Leaf Juice*, Glycerin, Niacinamide, Cucumis Sativus (Cucumber) Fruit Extract*, Lavandula Angustifolia (Lavender) Flower/Leaf/Stem Extract*, Chamomilla Recutita (Matricaria) Flower Extract*, Camellia Sinensis (White Tea) Leaf Extract*, Arnica Montana Flower Extract*, Salvia Officinalis (Sage) Oil, Mentha Piperita (Peppermint) Oil, Panthenol, Allantoin, Potassium Sorbate, Sodium Benzoate, Sodium PCA, Ethylhexylglycerin, Parfum**. *certified organic **our scent blend with natural and/or essential oils.

Questions or comments?

Call toll free 1-888-322-2466
Pacifica Beauty LLC Portland, Oregon